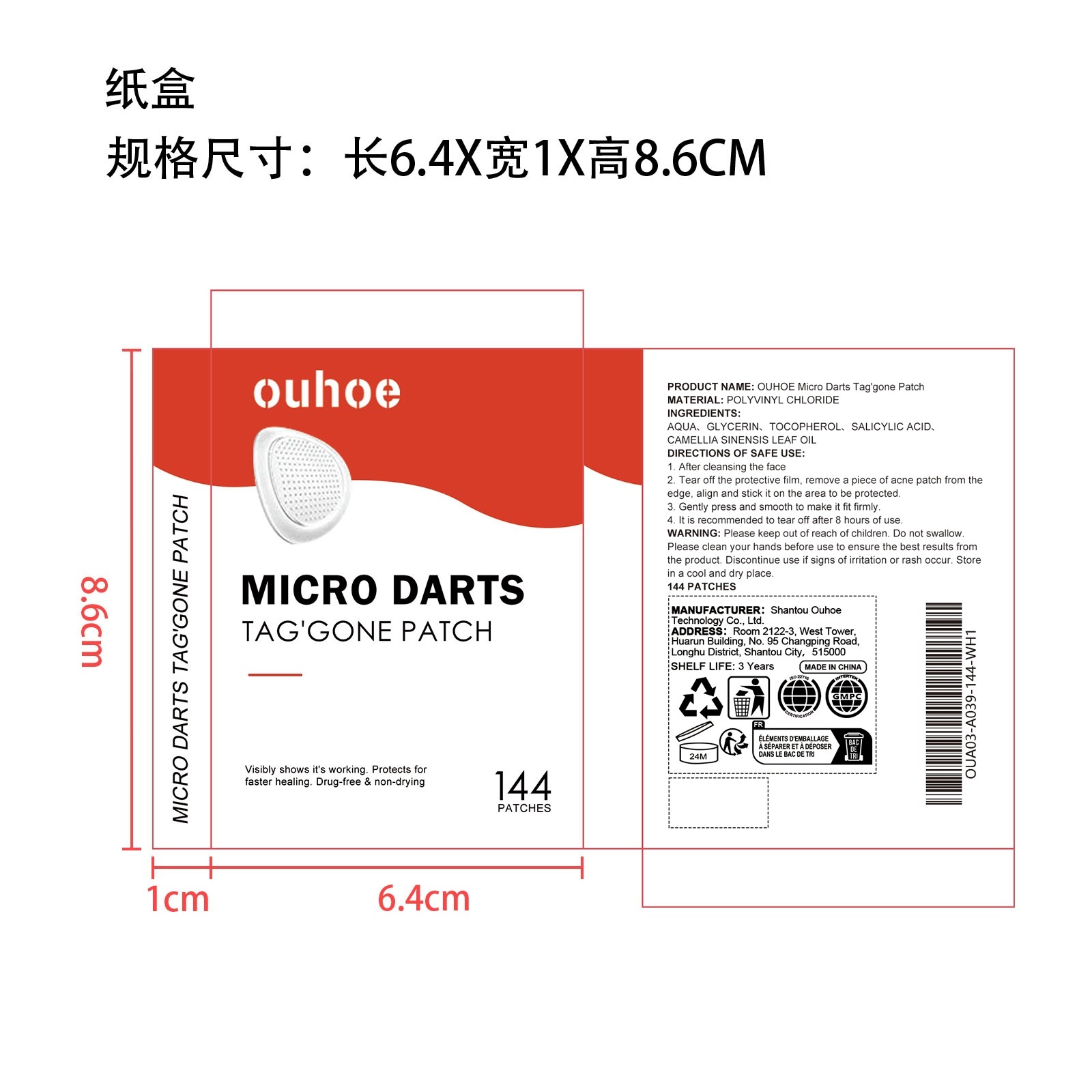 DRUG LABEL: OUHOE Micro Darts Tag gone Patch
NDC: 85163-004 | Form: PATCH
Manufacturer: Shantou Ouhoe Technology Co., Ltd.
Category: otc | Type: HUMAN OTC DRUG LABEL
Date: 20251127

ACTIVE INGREDIENTS: CAMELLIA SINENSIS LEAF OIL 0.02 mg/100 mg
INACTIVE INGREDIENTS: SALICYLIC ACID 0.02 mg/100 mg; GLYCERIN 1 mg/100 mg; TOCOPHEROL 0.1 mg/100 mg; AQUA 98.86 mg/100 mg

ACTIVE INGREDIENT

CAMELLIA SINENSIS LEAF OIL

WHEN USING

1. After cleansing the face

2. Tear off the protective film, remove a piece of acne patch from the edge, align and stick it on the area to be protected

3. Gently press and smooth to make it fit firmly

4. It is recommended to tear off after 8 hours of use

PURPOSE

1. This product is made of natural hydrocolloid, quickly repairs and removes skin tags such as moles, unclogs clogged pores, and effectively smoothes the skin

2. No pain, remove skin tags, restore skin health, balance water and oil, reduce redness/inflammation

3. Easy to use, no scars after use, specially designed for acne size

4. Suitable for all skin types with long-lasting effect

WARNINGS

Please keep out of reach of children. Do not swallow.Please clean your hands before use to ensure the best results from the product. Discontinue use if signs of irritation or rash occur. Store in a cool and dry place.

DO NOT USE

Discontinue use if signs of irritation or rash occur.

STOP USE

Discontinue use if signs of irritation or rash occur.

KEEP OUT OF REACH OF CHILDREN

Please keep out of reach of children. Do not swallow.

STORAGE AND HANDLING

Store in a cool and dry place.

INACTIVE INGREDIENT

AQUA、GLYCERIN、TOCOPHEROL、SALICYLIC ACID